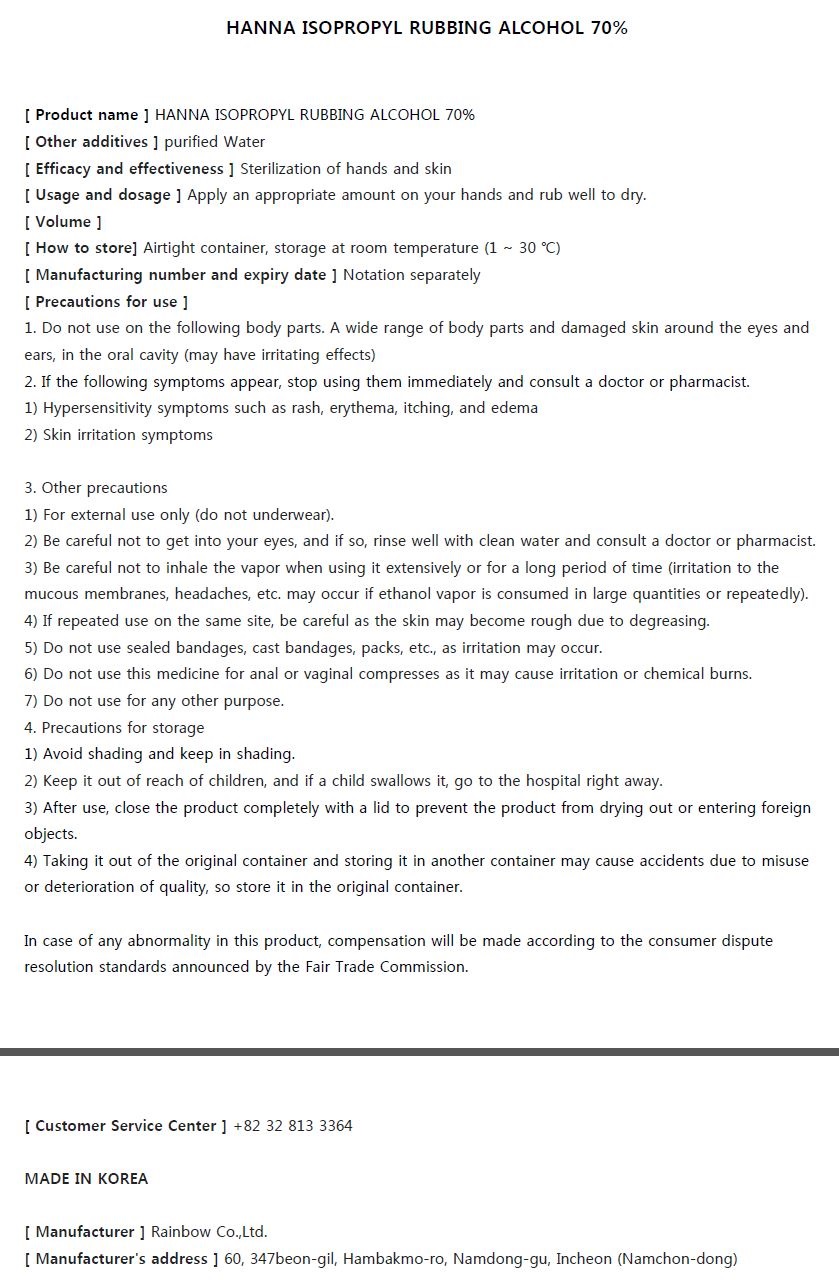 DRUG LABEL: HANNA ISOPROPYL RUBBING ALCOHOL 70%
NDC: 74247-0015 | Form: LIQUID
Manufacturer: Rainbow Co Ltd
Category: otc | Type: HUMAN OTC DRUG LABEL
Date: 20200725

ACTIVE INGREDIENTS: ISOPROPYL ALCOHOL 70 mL/100 mL
INACTIVE INGREDIENTS: WATER

Drug Facts

ACTIVE INGREDIENT

isopropyl alcohol

INACTIVE INGREDIENT

WATER,

PURPOSE

Sterilization of hands and skin

KEEP OUT OF REACH OF THE CHILDREN

INDICATIONS AND USAGE

Apply an appropriate amount on your hands and rub well to dry.

WARNINGS

1. Do not use on the following body parts. A wide range of body parts and damaged skin around the eyes and ears, in the oral cavity (may have irritating effects)
2. If the following symptoms appear, stop using them immediately and consult a doctor or pharmacist.
1) Hypersensitivity symptoms such as rash, erythema, itching, and edema
2) Skin irritation symptoms

DOSAGE AND ADMINISTRATION

for external use only